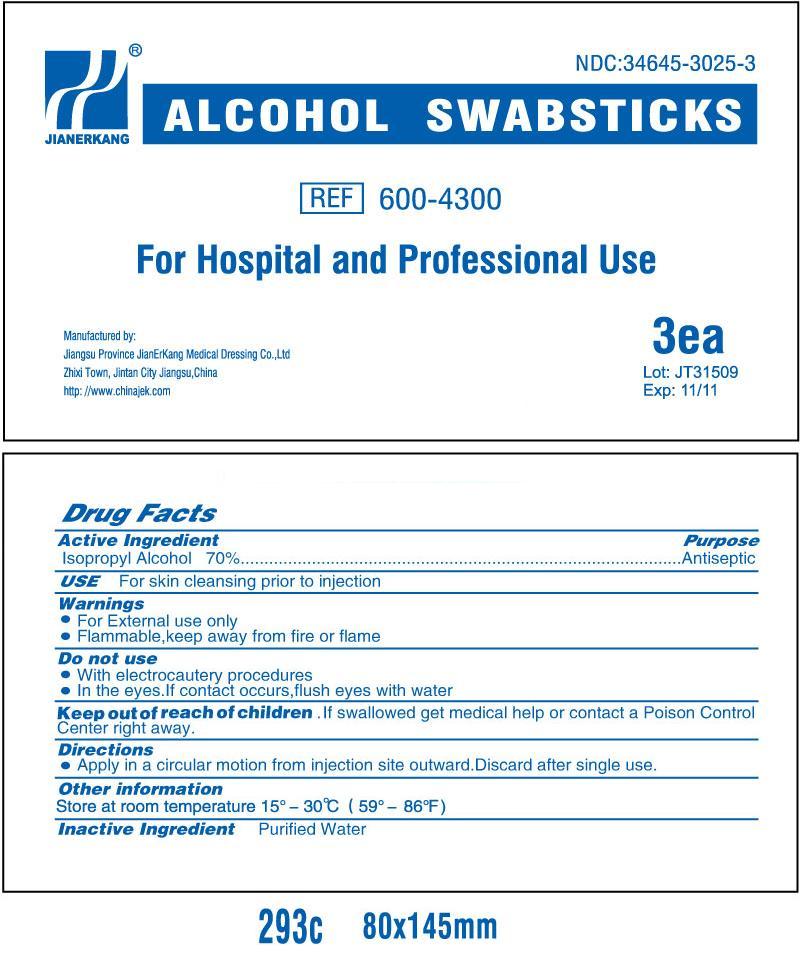 DRUG LABEL: Isopropyl Alcohol
NDC: 34645-3025 | Form: SWAB
Manufacturer: Jianerkang Medical Co., Ltd
Category: otc | Type: HUMAN OTC DRUG LABEL
Date: 20231023

ACTIVE INGREDIENTS: ISOPROPYL ALCOHOL 0.7 mL/1 mL
INACTIVE INGREDIENTS: WATER

Drug Facts

Active Ingredients

Isopropyl Alcohol 70%

Purpose

Antiseptic

Use

For skin cleansing prior to injection

Warnings

For external use only

Flammable, keep away from fire or flame

Do Not Use

with electrocautery procedures

in the eyes, if contact occurs, flush eyes with water

Keep out of reach of children

If swallowed, get medical help or contact Poison Control Center right away

Directions

Apply in a circular motion from injection site outward.Discard after single use.

Other Information

Store at room temperature 15 -30 C (59 -86 F)oooo

Inactive Ingredient

Purified Water